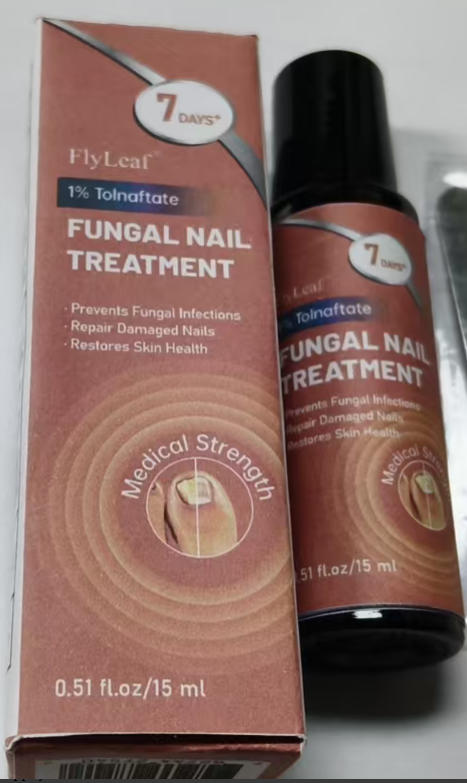 DRUG LABEL: FlyLeaf Fungal Nail Treatment
NDC: 87204-164 | Form: LIQUID
Manufacturer: Guangzhou Huixue Biotechnology Co., Ltd.
Category: otc | Type: HUMAN OTC DRUG LABEL
Date: 20260202

ACTIVE INGREDIENTS: TOLNAFTATE 1 mg/15 mL
INACTIVE INGREDIENTS: SQUALENE; TOCOPHEROL; EUCALYPTOL

ACTIVE INGREDIENT

Tolnaftate 1%

INACTIVE INGREDIENT

Aloe Vera Extract, Helianthus Annuus (Sunflower) Seed Oil, Prunus Armeniaca (Apricot) Kernel Oil, Melaleuca Alternifolia (Tea Tree) Leaf Oil, Eugenia Caryophyllus (Clove) Bud Oil, Lavandula Angustifolia (Lavender) Oil, Hakka Yu, Tocopherol, Origanum Vulgare Oil, Simmondsia Chinensis (Jojoba) Seed Oil, Eucalyptol, Tocopheryl Acetate, Squalene, Propolis Extract, Citrus Bergamia (Bergamot) Fruit Oil.

PURPOSE

Antifungal

INDICATIONS AND USAGE

For the treatment of nail fungus and associated symptoms, including discoloration, thickening, splitting, crumbling, and brittleness. . Relieves itching, scaling, cracking, burning, redness, soreness, irritation and discomfort. Hetps prevent most athtete's foot (dermatophytosis) with daily use.

WARNINGS

Warnings For external use only. De not use on children under 2 years of age unless directed by a doctor. When using this product, avoid contact with the eyes. tion occurs or if there is no improvement within 4 weeks. Keep out of reach of children. If swallowed, get medical help or contact a Poison Control Center right away.

Keep out of reach of children. If swallowed, get medical help or contact a Poison Control Center right away.
Store at room temperature. Avoid direct sunlight.

WHEN USING

1. Clean the affected area and dry thoroughly. Apply a thin layer of the product over affected area twice daily (morning and night) or as directed by a doctor. Gently file the nail to make it thinner and remove debris, being cautious not to harm the nail bed. For best results, file nails every 2-3 days. 2. Supervise children in the use of this product. For athlete's foot: Pay special attention to spaces between the toes; wear well-fitting, ventilated shoes, and change shoes and socks at least once daily. To prevent athlete's foot, apply once or twice daily (morning and/or night). For toe fungus, apply to skin around the nail and cuticle. Visible improvement may be seen in as little as 7 days. Continue regular use to help prevent fungus regrowth.

DO NOT USE

For external use only. Do not use on children under 2 years of age unless directed by a doctor. When using this product, avoid contact with the eyes. Stop use and ask a doctor if irritation occurs or if there is no improvement within 4 weeks.

STOP USE

irritation occurs or if there is no improvement within 4 weeks.

DOSAGE AND ADMINISTRATION

Twice each day,(1ml)each time.7 days supply